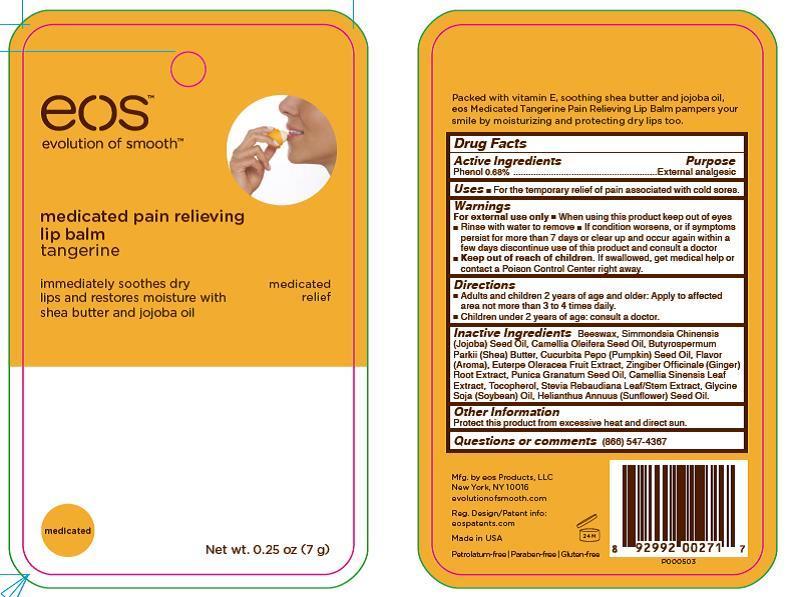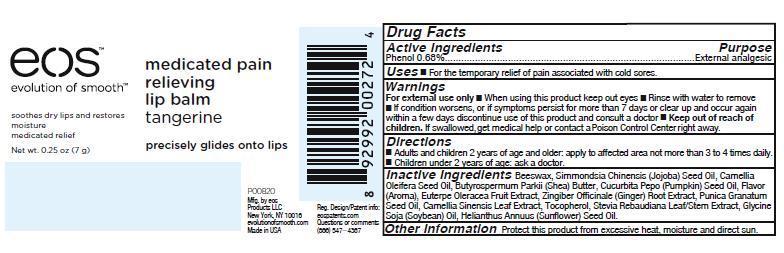 DRUG LABEL: eos Medicated Pain Relieving Lip Balm
NDC: 70170-0003 | Form: STICK
Manufacturer: eos Products LLC
Category: otc | Type: HUMAN OTC DRUG LABEL
Date: 20151102

ACTIVE INGREDIENTS: PHENOL 0.68 g/7 g
INACTIVE INGREDIENTS: JOJOBA OIL; YELLOW WAX; SHEA BUTTER; PUMPKIN SEED OIL; CAMELLIA OIL; TOCOPHEROL; SOYBEAN OIL; POMEGRANATE SEED OIL; SUNFLOWER OIL; GREEN TEA LEAF; GINGER; ACAI; TANGERINE; STEVIA REBAUDIUNA LEAF

eos Medicated Pain Relieving Lip Balm

Drug Facts

Active Ingredients Purpose

Phenol 0.68% External Analgesic

Uses

For the temporary relief of pain associated with cold sores.

Warnings

For external use only

Keep out of reach of children. If swallowed, get medical help or contact a Poison Control Center right away.

When using this product keep out of eyes. Rinse with water to remove.

STOP USE

If condition worsens, or if symptoms persist for more than 7 days or clear up and occur again within a few days discontinue use of this product and consult a doctor.

Directions

Adults and children 2 years of age and older: Apply to affected area not more than 3 to 4 times daily.
Children under 2 years of age: consult a doctor.

Inactive Ingredients

Beeswax, Simmondsia Chinensis (Jojoba) Seed Oil, Camellia Oleifera Seed Oil, Butyrospermum Parkii (Shea) Butter, Cucurbita Pepo (Pumpkin) Seed Oil, Flavor (Aroma), Euterpe Oleracea Fruit Extract, Zingiber Officinale (Ginger) Root Extract, Punica Granatum Seed Oil, Camellia Sinensis Leaf Extract, Tocopherol, Stevia Rebaudiana Leaf/Stem Extract, Glycine Soja (Soybean) Oil, Helianthus Annuus (Sunflower) Seed Oil.

Other Information

Protect this product from excessive heat and direct sun.

Questions or Comments

(866) 547-4367

Principle Display Panel - 0.25 oz BLISTER PACK

eos

Medicated Pain Relieving

Lip Balm

Tangerine

Net wt. 0.25 oz (7 g)

Principle Display Panel - 0.25 oz CELLO PACK

eos
Medicated Pain Relieving
Lip Balm
Tangerine
Net wt. 0.25 oz (7 g)